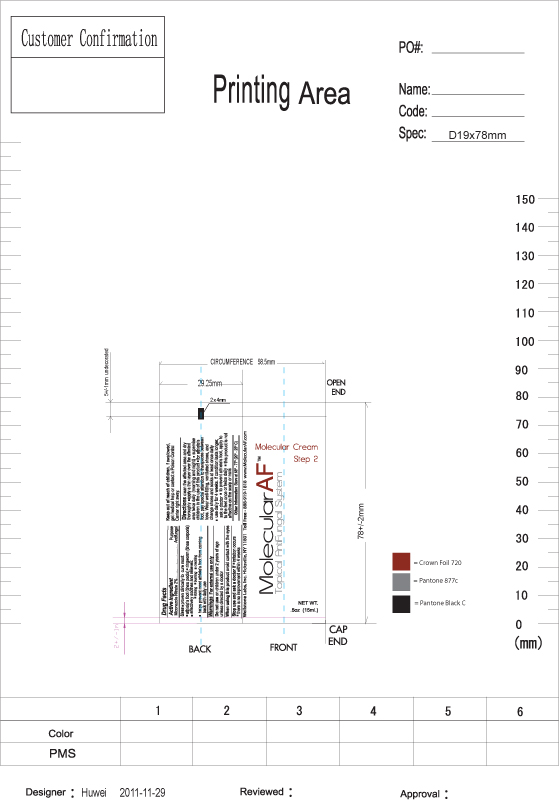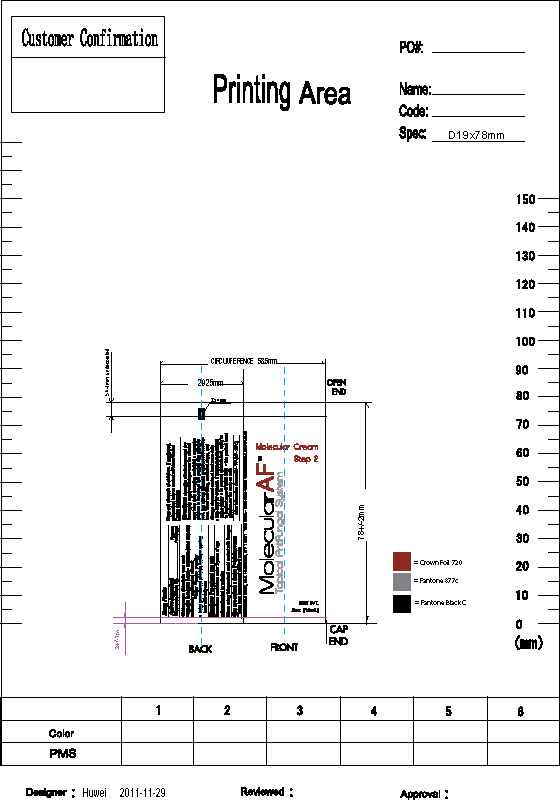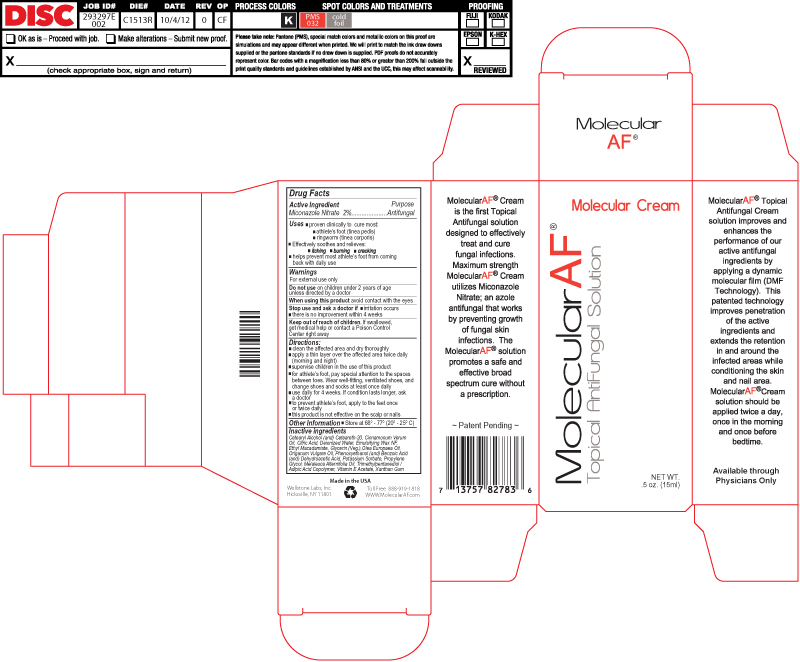 DRUG LABEL: Molecular AF Molecular Cream
NDC: 76348-402 | Form: CREAM
Manufacturer: Renu Laboratories, Inc.
Category: otc | Type: HUMAN OTC DRUG LABEL
Date: 20220117

ACTIVE INGREDIENTS: Miconazole Nitrate 0.3 g/14 g
INACTIVE INGREDIENTS: Benzoic Acid; Water; Xanthan Gum; Glycerin; CETOSTEARYL ALCOHOL; POLAWAX POLYSORBATE; TRIMETHYL-1,3-PENTANEDIOL; Tea Tree Oil; Cinnamon Oil; Ethyl Macadamiate; TROLAMINE; Phenoxyethanol; Oregano Leaf Oil; POLYOXYL 20 CETOSTEARYL ETHER; Propylene Glycol; Olive Oil; .ALPHA.-TOCOPHEROL ACETATE

Molecular AF Molecular Cream

Active Ingredient

Miconazole Nitrate 2%

Purpose

Antifungal

Warnings

For external use only

Do not use on children under 2 years of age unless directed by a doctor

When using this product avoid contact with the eyes

Stop use and ask a doctor if

- irritation occurs
- there is no improvement with 4 weeks

Keep out of reach of children. If swallowed, get medical help or contact a Poison Control Center right away

Stop use and ask a doctor if

- irritation occurs
- there is no improvement within 4 weeks

Keep out of reach of children. If swallowed,

get medical help or contact a Poison Control

Center right away

Directions

- clean the affected area and dry thoroughly
- apply a thin layer over the affected area twice daily (morning and night)
- supervise children in the use of this product
- for athlete's foot, pay special attention to the spaces between toes. Wear well-fitting, ventilated shoes, and
  change shoes and socks at least once daily.
- use daily for 4 weeks. If condition lasts longer, ask a doctor
- to prevent athlete's foot, apply to the feet once or twice daily
- this product is not effective on the scalp or nails

Other Information

- Store at 68° - 77º (20º - 25º C)

Inactive Ingredients

Cetearyl Alcohol, Ceteareth-20, Cinnamonum Verum Oil, Citric Acid, Deionized Water, Emulsifying Wax NF, Ethyl Macadamiate,

Glycerin (Veg.), Melaleuca Alternifolia Oil, Olea Europaea Oil, Origanum Vulgare Oil, Phenoxyethanol, Benzoic Acid,

Dehydroacetic Acid, Propylene Glycol, Trimethylpentanediol / Adipic Acid Copolymer, Vitamin E Acetate, Xanthan Gum

Directions:

- clean the affected area and dry thoroughly
- apply a thin layer over the affected area twice daily (morning and night)
- supervise children in the use of this product
- for athlete's foot, pay special attention to the spaces between toes..
  Wear well-fitting, ventilated shoes, and change shoes and socks at least once daily
- use daily for 4 weeks. If condition lasts longer, as a doctor
- to prevent athlete's foot, apply to the feet once or twice daily
- this product is not effective on the scalp or nails